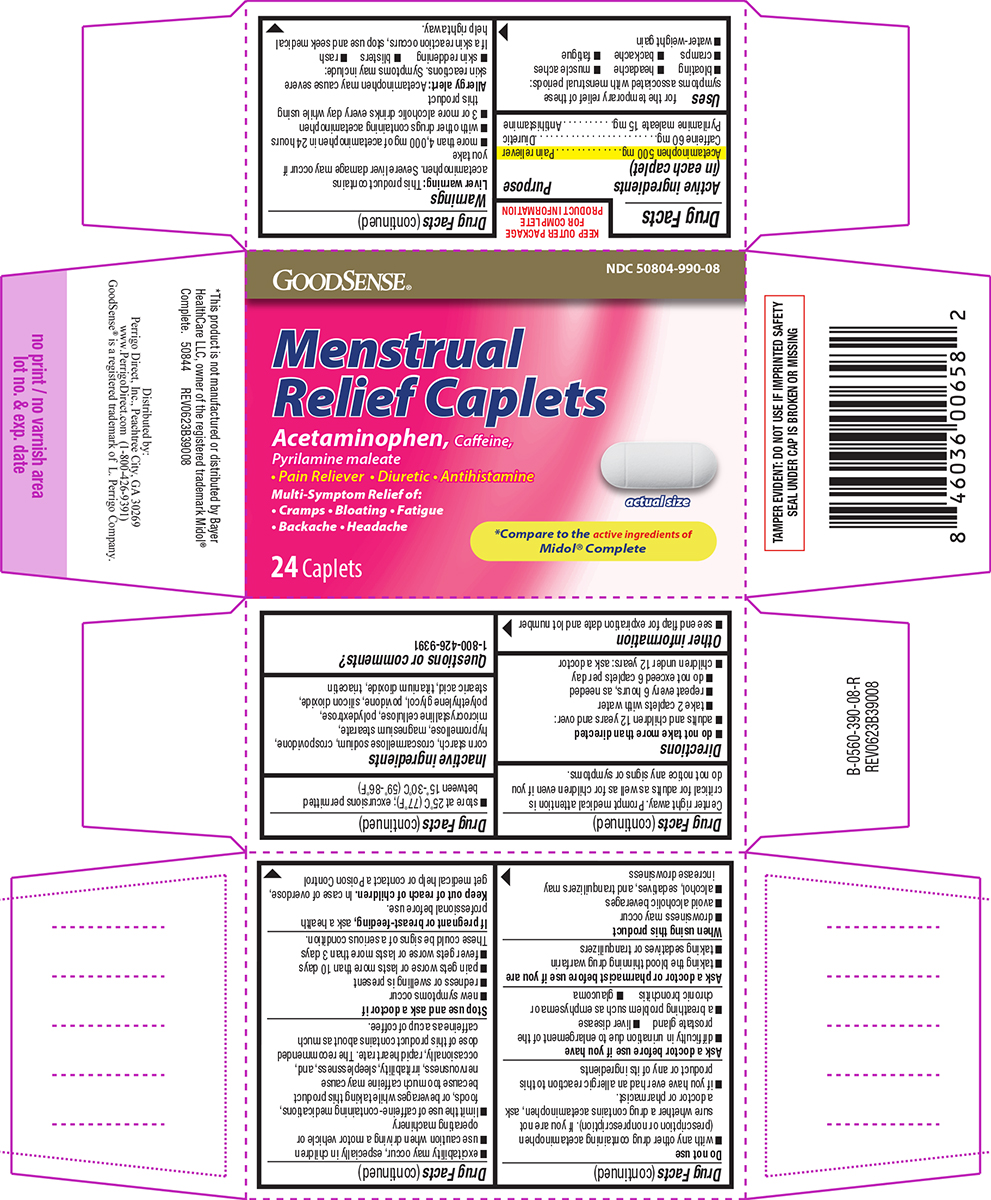 DRUG LABEL: Menstrual Relief
NDC: 50804-990 | Form: TABLET, FILM COATED
Manufacturer: Geiss, Destin & Dunn Inc.
Category: otc | Type: HUMAN OTC DRUG LABEL
Date: 20260206

ACTIVE INGREDIENTS: ACETAMINOPHEN 500 mg/1 1; CAFFEINE 60 mg/1 1; PYRILAMINE MALEATE 15 mg/1 1
INACTIVE INGREDIENTS: STARCH, CORN; CROSCARMELLOSE SODIUM; CROSPOVIDONE, UNSPECIFIED; HYPROMELLOSE, UNSPECIFIED; MAGNESIUM STEARATE; MICROCRYSTALLINE CELLULOSE; POLYDEXTROSE; POLYETHYLENE GLYCOL, UNSPECIFIED; POVIDONE, UNSPECIFIED; SILICON DIOXIDE; STEARIC ACID; TITANIUM DIOXIDE; TRIACETIN

GoodSense 44-390

Active ingredients (in each caplet)

Acetaminophen 500 mg
Caffeine 60 mg
Pyrilamine maleate 15 mg

Purpose

Pain reliever
Diuretic
Antihistamine

Uses

for the temporary relief of these symptoms associated with menstrual periods:

- bloating
- headache
- muscle aches
- cramps
- backache
- fatigue
- water-weight gain

Warnings

Liver warning: This product contains acetaminophen. Severe liver damage may occur if you take

- more than 4,000 mg of acetaminophen in 24 hours
- with other drugs containing acetaminophen
- 3 or more alcoholic drinks every day while using this product

Allergy alert: Acetaminophen may cause severe skin reactions. Symptoms may include:

- skin reddening
- blisters
- rash

If a skin reaction occurs, stop use and seek medical help right away.

Do not use

- with any other drug containing acetaminophen (prescription or nonprescription). If you are not sure whether a drug contains acetaminophen, ask a doctor or pharmacist.
- if you have ever had an allergic reaction to this product or any of its ingredients

Ask a doctor before use if you have

- difficulty in urination due to enlargement of the prostate gland
- liver disease
- a breathing problem such as emphysema or chronic bronchitis
- glaucoma

Ask a doctor or pharmacist before use if you are

- taking the blood thinning drug warfarin
- taking sedatives or tranquilizers

When using this product

- drowsiness may occur
- avoid alcoholic beverages
- alcohol, sedatives, and tranquilizers may increase drowsiness
- excitability may occur, especially in children
- use caution when driving a motor vehicle or operating machinery
- limit the use of caffeine-containing medications, foods, or beverages while taking this product because too much caffeine may cause nervousness, irritability, sleeplessness, and, occasionally, rapid heart rate. The recommended dose of this product contains about as much caffeine as a cup of coffee.

Stop use and ask a doctor if

- new symptoms occur
- redness or swelling is present
- pain gets worse or lasts more than 10 days
- fever gets worse or lasts more than 3 days

These could be signs of a serious condition.

If pregnant or breast-feeding,

ask a health professional before use.

Keep out of reach of children.

In case of overdose, get medical help or contact a Poison Control Center right away. Prompt medical attention is critical for adults as well as for children even if you do not notice any signs or symptoms.

Directions

- do not take more than directed
- adults and children 12 years and over:
  - take 2 caplets with water
  - repeat every 6 hours, as needed
  - do not exceed 6 caplets per day
- children under 12 years: ask a doctor

Other information

- see end flap for expiration date and lot number
- store at 25°C (77°F); excursions permitted between 15°-30°C (59°-86°F)

Inactive ingredients

corn starch, croscarmellose sodium, crospovidone, hypromellose, magnesium stearate, microcrystalline cellulose, polydextrose, polyethylene glycol, povidone, silicon dioxide, stearic acid, titanium dioxide, triacetin

Questions or comments?

1-800-426-9391

Principal Display Panel

GOODSENSE®

NDC 50804-990-08

Menstrual
Relief Caplets

Acetaminophen, Caffeine,
Pyrilamine maleate
• Pain Reliever • Diuretic • Antihistamine

Multi-Symptom Relief of:
• Cramps • Bloating • Fatigue
• Backache • Headache

24 Caplets

actual size

*Compare to the active ingredients of
Midol® Complete

TAMPER EVIDENT: DO NOT USE IF IMPRINTED SAFETY
SEAL UNDER CAP IS BROKEN OR MISSING

*This product is not manufactured or distributed by Bayer
HealthCare LLC, owner of the registered trademark Midol®
Complete. 50844 REV0623B39008

Distributed by:
Perrigo Direct, Inc., Peachtree City, GA 30269
www.PerrigoDirect.com (1-800-426-9391)
GoodSense® is a registered trademark of L. Perrigo Company.

Good Sense 44-390